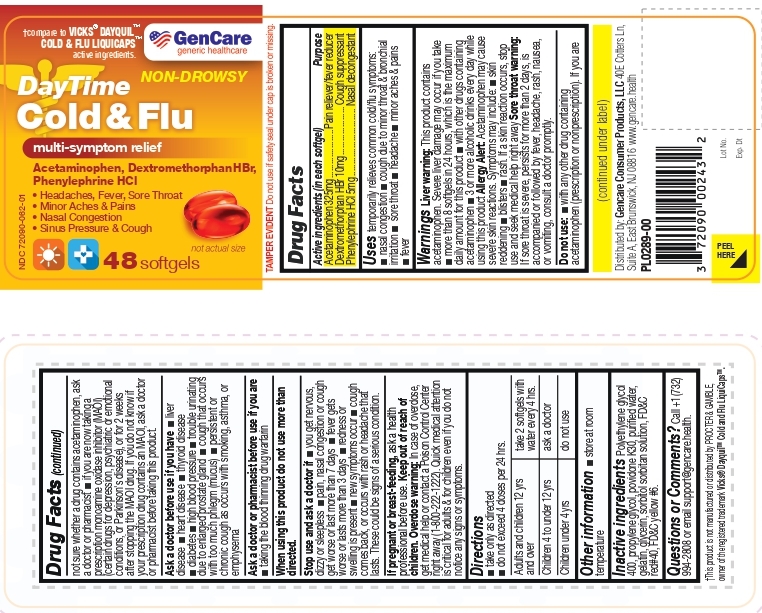 DRUG LABEL: Gencare DayTime Cold and Flu Softgel
NDC: 72090-062 | Form: CAPSULE, LIQUID FILLED
Manufacturer: Pioneer Life Sciences, LLC
Category: otc | Type: HUMAN OTC DRUG LABEL
Date: 20260213

ACTIVE INGREDIENTS: ACETAMINOPHEN 325 mg/1 1; DEXTROMETHORPHAN HYDROBROMIDE 10 mg/1 1; PHENYLEPHRINE HYDROCHLORIDE 5 mg/1 1
INACTIVE INGREDIENTS: POLYETHYLENE GLYCOL 400; PROPYLENE GLYCOL; POVIDONE; Gelatin; Sorbitol; GLYCERIN; FD&C RED NO. 40; FD&C YELLOW NO. 6

Gencare DayTime Cold and Flu Softgel (Acetaminophen 325mg, Dextromethorphan HBr 10mg, Phenylephrine HCl 5mg)

Active ingredients (in each softgel)

Acetaminophen 325mg

Dextromethorphan HBr 10mg

Phenylephrine HCl 5mg

Purpose

Acetaminophen 325mg.....................Pain reliever/fever reducer
Dextromethorphan HBr 10mg..................... Cough suppressant
Phenylephrine HCl 5mg ............................. Nasal decongestant

Uses:

temporarily relieves common cold/flu symptoms:
■ nasal congestion

■ cough due to minor throat & bronchial irritation

■ sore throat

■ headache

■ minor aches & pains

■ fever

Warning

Liver warning: This product contains acetaminophen. Severe liver damage may occur if you take
■ more than 8 softgels in 24 hours, which is the maximum daily amount for this product

■ with other drugs containing acetaminophen

■ 3 or more alcoholic drinks every day while using this product

Allergy Alert: Acetaminophen may cause severe skin reactions. Symptoms may include:

■ skin reddening

■ blisters

■ rash.

If a skin reaction occurs, stop use and seek medical help right away

Sore throat warning:
If sore throat is severe, persists for more than 2 days, is accompanied or followed by fever, headache, rash, nausea, or vomiting, consult a doctor promptly.

Do not use:

- with any other drug containing acetaminophen (prescription or nonprescription). If you are not sure whether a drug contains acetaminophen, ask a doctor or pharmacist
- if you are now taking a prescription monoamine oxidase inhibitor (MAOI) (certain drugs for depression, psychiatric or emotional
  conditions, or Parkinson's disease), or for 2 weeks after stopping the MAOI drug. If you do not know if your prescription drug contains an MAOI, ask a doctor or pharmacist before taking this product.

Ask a doctor before use if you have

■ liver disease

■ heart disease

■ thyroid disease

■ diabetes

■ high blood pressure

■ trouble urinating due to enlarged prostate gland

■ cough that occurs with too much phlegm (mucus)

■ persistent or chronic cough as occurs with smoking, asthma, or emphysema

Ask a doctor or pharmacist before use if you are

- taking the blood thinning drug warfarin

When using this product do not use more than directed.

Stop use and ask a doctor if

- you get nervous, dizzy or sleepless
- pain, nasal congestion or cough get worse or last more than 7 days
- fever gets worse or lasts more than 3 days
- redness or swelling is present
- new symptoms occur
- cough comes back, or occurs with rash or headache that lasts. These could be signs of a serious condition.

PREGNANCY OR BREAST FEEDING

If pregnant or breast-feeding, ask a health professional before use.

Keep out of reach of children.

OVERDOSAGE

Overdose warning: In case of overdose, get medical help or contact a Poison Control Center right away (1-800-222-1222). Quick medical attention is critical for adults & for children even if you do not notice any signs or symptoms.

Directions

■ take only as directed

■ do not exceed 4 doses per 24 hrs.

Adults and children 12 yrs and over | take 2 softgels with water every 4 hrs.
Children 4 to under 12 yrs | ask a doctor
Children under 4 yrs | do not use

Other information

■ store at room temperature

Inactive ingredients

Polyethylene glycol 400, propylene glycol, povidone K30, purified water, gelatin, glycerin, sorbitol sorbitan solution, FD&C red#40, FD&C yellow #6.

Questions or Comments?

Call +1 (732) 994-2808 or email support@gencare.health.

This product is not manufactured or distributed by PROCTER & GAMBLE, owner of the registered trademark Vicks® Dayquil™ Cold and Flu LiquiCaps™.

Distributed by: Gencare Consumer Products, LLC
40E Cotters Ln, Suite A, East Brunswick, NJ 08816